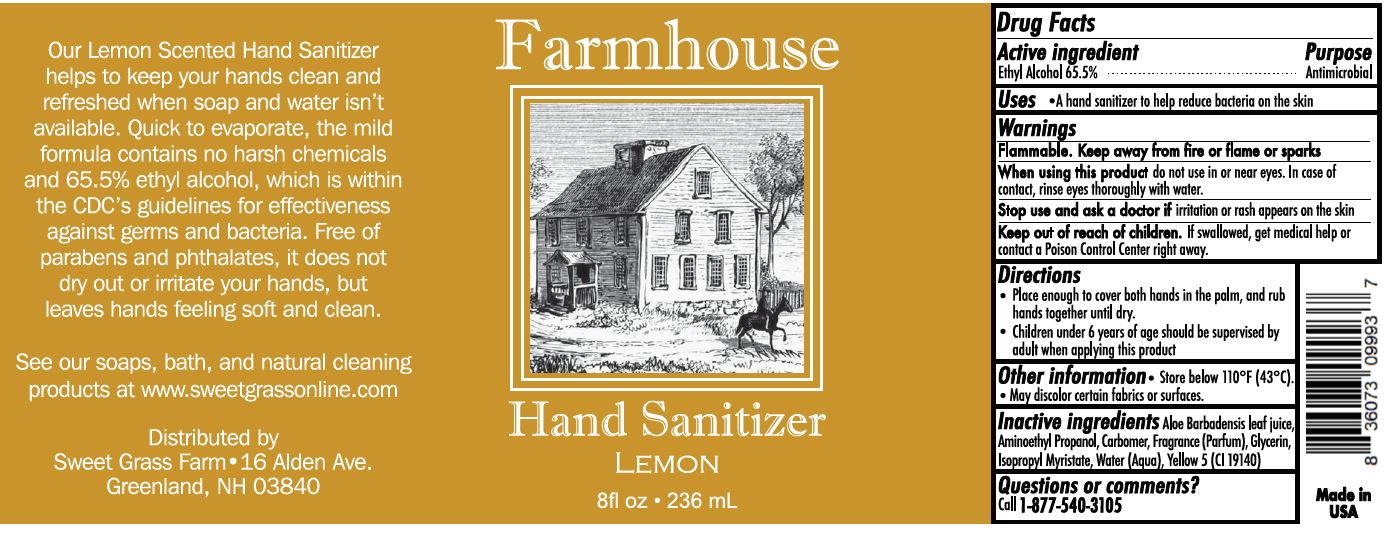 DRUG LABEL: Hand Sanitizer

NDC: 76776-001 | Form: LIQUID
Manufacturer: Sweet Grass Farm
Category: otc | Type: HUMAN OTC DRUG LABEL
Date: 20220114

ACTIVE INGREDIENTS: ALCOHOL 65.5 mL/100 mL
INACTIVE INGREDIENTS: ALOE; GLYCERIN; WATER; ISOPROPYL MYRISTATE; CARBOMER 940; AMINOMETHYLPROPANOL

Drug Facts

Active Ingredient Purpose

Elhyl Alcohol 6S.S% Antimicrobial

Warning

Flammable. Keep away from fire or home or sparks
When Using this product do not use in or near eyes. In case of contact, rinse eyes thoroughly with water .
Stop use and ask a doctor if irritotion or rush appears on the skin

Keep out of reoch of children.

If swollowed, get medical help or contoct a poison Contact Center right away.

Uses

To help reduce bacteria on the skin

Direction

- Place enough to cover both hands in the palm, and rub hands together until dry.
- Children under 6 years of age should be supervised by adult when applying this product

Other information

- Store below 110^0F (43^0C)
- May discolor certan fabrics or surfaces

Inactive ingredients

Water (Aqua), Glycerin, Aloe Barbadensis Leaf Juice, Isopropyl Myristate, Fragrance (Parfum), Carbomer, Aminomethyl Propanol, Yellow 5 (CI 19140).

Questions or comments?

Call 1-877-540-3105